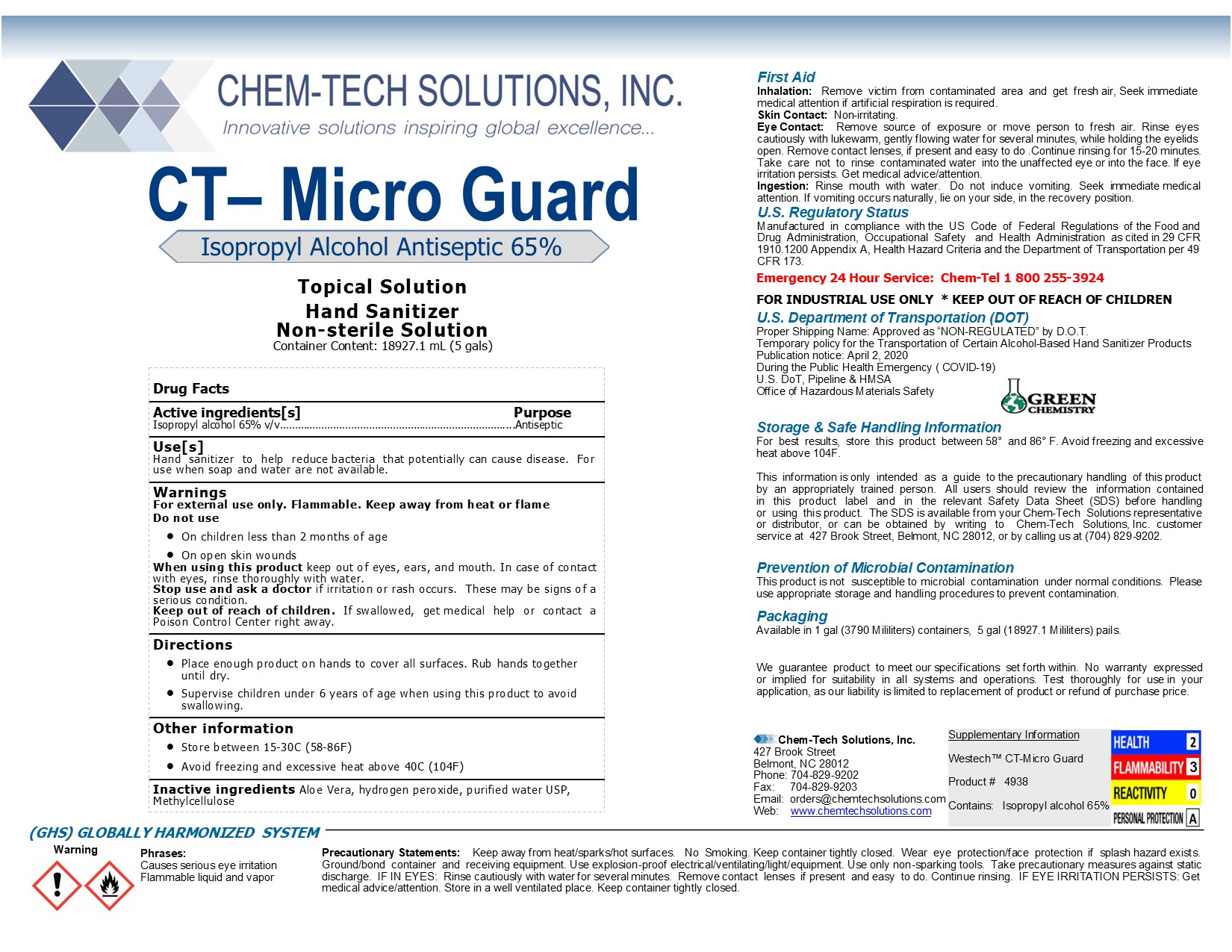 DRUG LABEL: CT-Mirco Guard
NDC: 75059-4938 | Form: LIQUID
Manufacturer: Chem-Tech Solutions, Inc.
Category: otc | Type: HUMAN OTC DRUG LABEL
Date: 20220118

ACTIVE INGREDIENTS: ISOPROPYL ALCOHOL 65 mL/100 mL
INACTIVE INGREDIENTS: ALOE VERA LEAF 1.45 mL/100 mL; WATER; HYDROGEN PEROXIDE 0.125 mL/100 mL; METHYLCELLULOSE, UNSPECIFIED 1 mL/100 mL

Active ingredients[s] Purpose

Isopropyl alcohol 65% v/v…………………………………………………………………....Antiseptic

Do not use

· On children less than 2 months of age

· On open skin wounds

Keep out of reach of children. If swallowed, get medical help or contact a Poison Control Center right away.

Active ingredients[s] Purpose

Isopropyl alcohol 65% v/v…………………………………………………………………....Antiseptic

Stop use and ask a doctor if irritation or rash occurs. These may be signs of a serious condition.

When using this product keep out of eyes, ears, and mouth. In case of contact with eyes, rinse thoroughly with water.

Other information

· Store between 15-30C (58-86F)

· Avoid freezing and excessive heat above 40C (104F)

Warnings

For external use only. Flammable. Keep away from heat or flame

INACTIVE INGREDIENT

Inactive ingredients Aloe Vera, hydrogen peroxide, purified water USP, Methylcellulose

Warning

Phrases:

Causes serious eye irritation

Flammable liquid and vapor

INDICATIONS AND USAGE

Use[s]

Hand sanitizer to help reduce bacteria that potentially can cause disease. For use when soap and water are not available.

Directions

· Place enough product on hands to cover all surfaces. Rub hands together until dry.

· Supervise children under 6 years of age when using this product to avoid swallowing.

PACKAGE LABEL

CT– Micro Guard

Isopropyl Alcohol Antiseptic 65%

Topical Solution

Hand Sanitizer

Non-sterile Solution

Container Content: 18927.1 ML (5 gals)